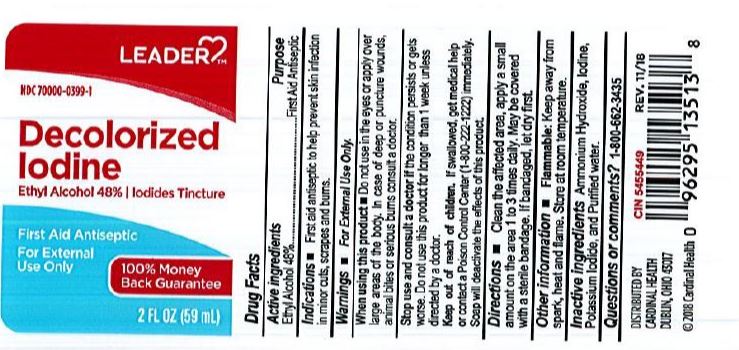 DRUG LABEL: Leader Decolorized Iodine
NDC: 70000-0399 | Form: LIQUID
Manufacturer: Cardinal Health, 110 dba Leader
Category: otc | Type: HUMAN OTC DRUG LABEL
Date: 20240513

ACTIVE INGREDIENTS: ALCOHOL 0.48 mL/1 mL
INACTIVE INGREDIENTS: POTASSIUM IODIDE; AMMONIA; WATER; IODINE

LEADER Decolorized Iodine

DOSAGE AND ADMINISTRATION

Clean the affected area, apply a small amount on the area 1 to 3 times daily. May be covered with a sterile bandage. If bandaged, let dry first.

ACTIVE INGREDIENT

Ethyl Alcohol 48%

INDICATIONS AND USAGE

First aid antiseptic to help prevent skin infection in minor cuts, scrapes and burns.

WARNINGS

For External Use Only.

When using this product:

Do not use in the eyes or apply over large areas of the body. In case of deep or puncture wounds, animal bites or serious burns consult a doctor.

Keep out of reach of children.If swallowed, get medical help or contact a Poison Control Center (1-800-222-1222) immediately. Soap will deactivate the effects of this product.

INACTIVE INGREDIENT

- Ammonium Hydroxide
- Iodine
- Potassium Iodide
- Purified Water

PURPOSE

First Aid Antiseptic